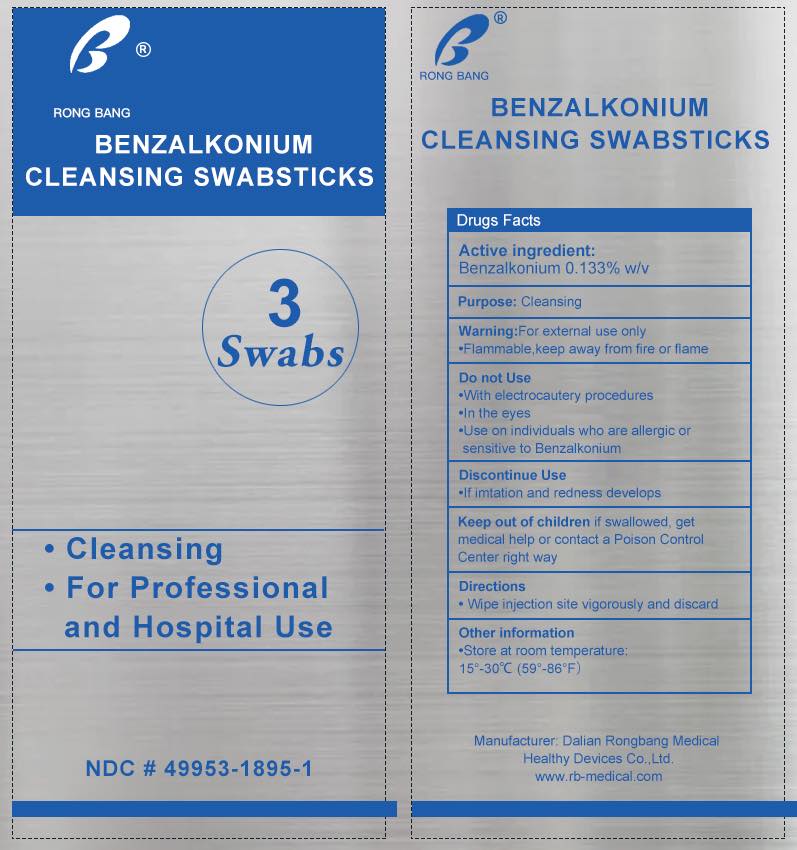 DRUG LABEL: RONGBANG BZK Cleansing Swabstick
NDC: 49953-1895 | Form: SWAB
Manufacturer: Dalian Rongbang Medical Healthy Devices Co., Ltd.
Category: otc | Type: HUMAN OTC DRUG LABEL
Date: 20231228

ACTIVE INGREDIENTS: BENZALKONIUM CHLORIDE 0.133 mg/100 g
INACTIVE INGREDIENTS: WATER

Dalian Rongbang Benzalkonium Cleansing Swabsitcks

PURPOSE

Cleansing

Warning:

- For external use only
- Flammable,keep away from fire or flame

Do not Use

·With electrocautery procedures

·Do not use in the eyes

·Do not use on individuals who are allergic or sensitive to Benzalkonium

Discontinue Use

·if inflamation and redness develops

Ask a doctor before use if you have deep or puncture wounds, animal bites, or serious burns.

KEEP OUT OF REACH OF CHILDREN

Keep out of children if swallowed, get medical help or contact a Poison Control Center right way

Directions

Wipe injection site vigorously and discard

Use

Used for cleansing

Other information

Store at room temperature: 15°-30℃ (59°-86°F）

ACTIVE INGREDIENT

Benzalkonium 0.133% w/v

INACTIVE INGREDIENT

Water